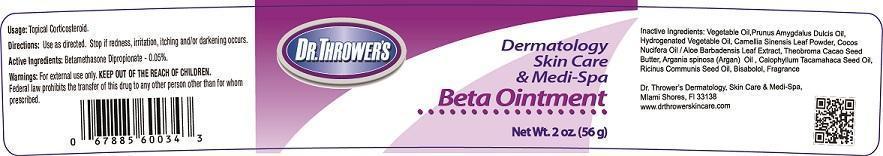 DRUG LABEL: DR. THROWERS BETA
NDC: 69299-202 | Form: OINTMENT
Manufacturer: DR. THROWER'S SKINCARE, INC.
Category: prescription | Type: HUMAN PRESCRIPTION DRUG LABEL
Date: 20150522

ACTIVE INGREDIENTS: BETAMETHASONE 0.05 g/100 g
INACTIVE INGREDIENTS: CORN OIL; ALMOND OIL; HYDROGENATED SOYBEAN OIL; GREEN TEA LEAF; COCONUT OIL; ALOE VERA LEAF; COCOA BUTTER; ARGAN OIL; CALOPHYLLUM TACAMAHACA SEED OIL; CASTOR OIL; .ALPHA.-BISABOLOL, (+)-

DIRECTIONS:

USE AS DIRECTED. STOP USE IF REDNESS, IRRITATION, ITCHING AND/OR DARKENING OCCURS.

INGREDIENTS:

VEGETABLE OIL, PRUNUS AMYGDALUS OIL, HYDROGENATED VEGETABLE OIL, CAMEMILLIA SINENSIS LEAF POWDER, COCOS NUCIFERA OIL / ALOE BARBEDENSIS LEAF EXTRACT, THEOBROMA CACAO SEED BUTTER, ARGENIA SPINOSA (ARGAN) OIL, CALOPHYLLUM TACAMAHACA SEED OIL, RICINUS COMMUNIS SEED OIL, BISABOLOL, FRAGRANCE

WARNINGS

FOR EXTERNAL USE ONLY. KEEP OUT OF REACH OF CHILDREN. FEDERAL LAW PROHIBITS THE TRANSFER OF THIS DRUG TO ANY OTHER PERSON OTHER THAN FOR WHOM PRESCRIBED.